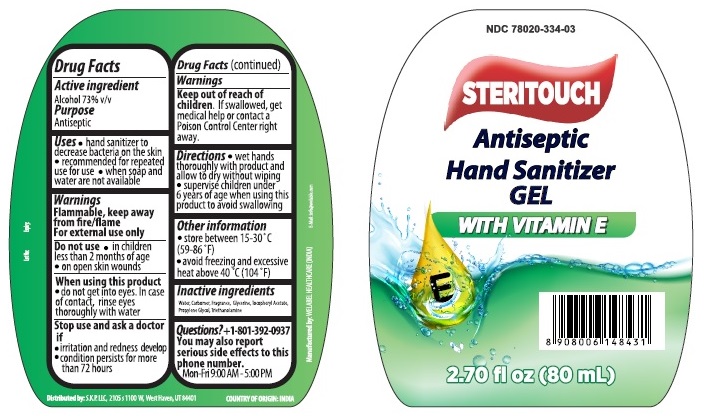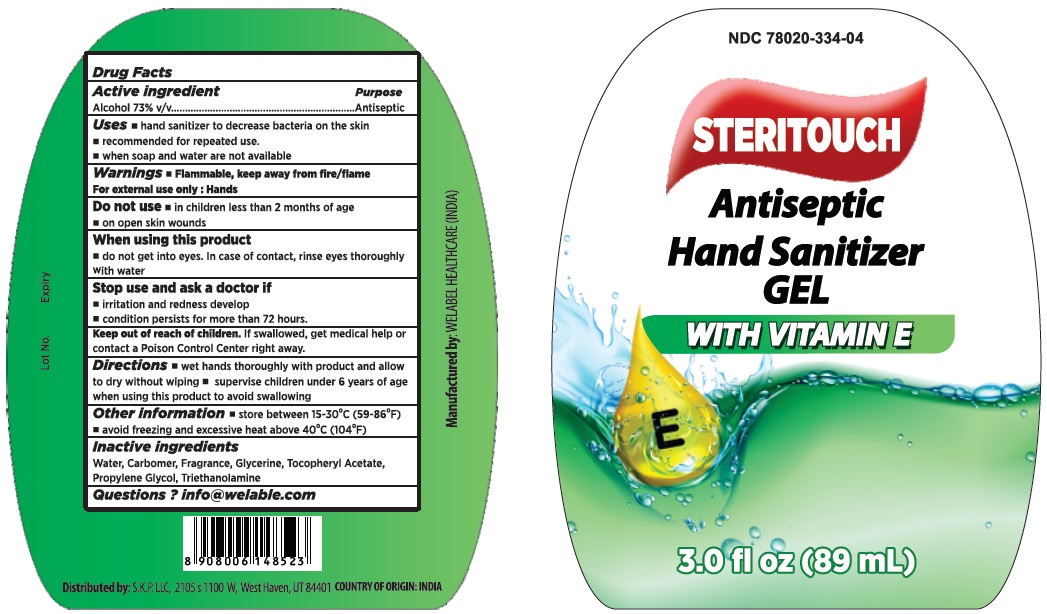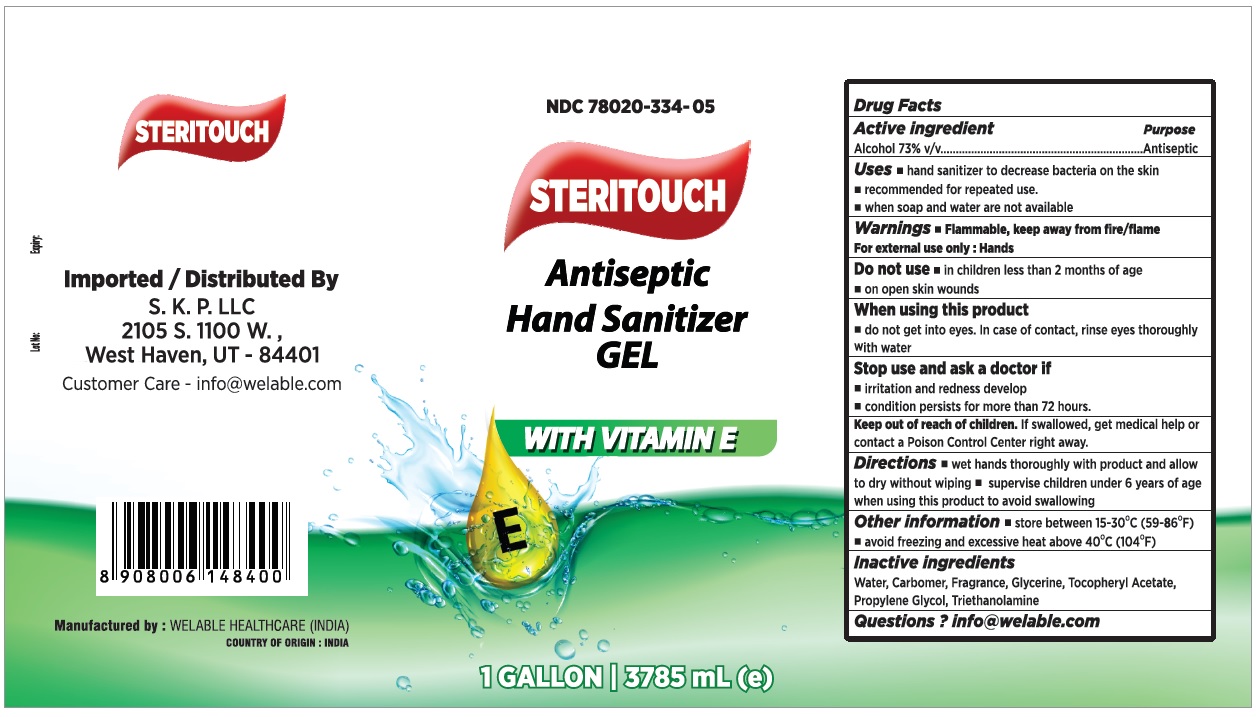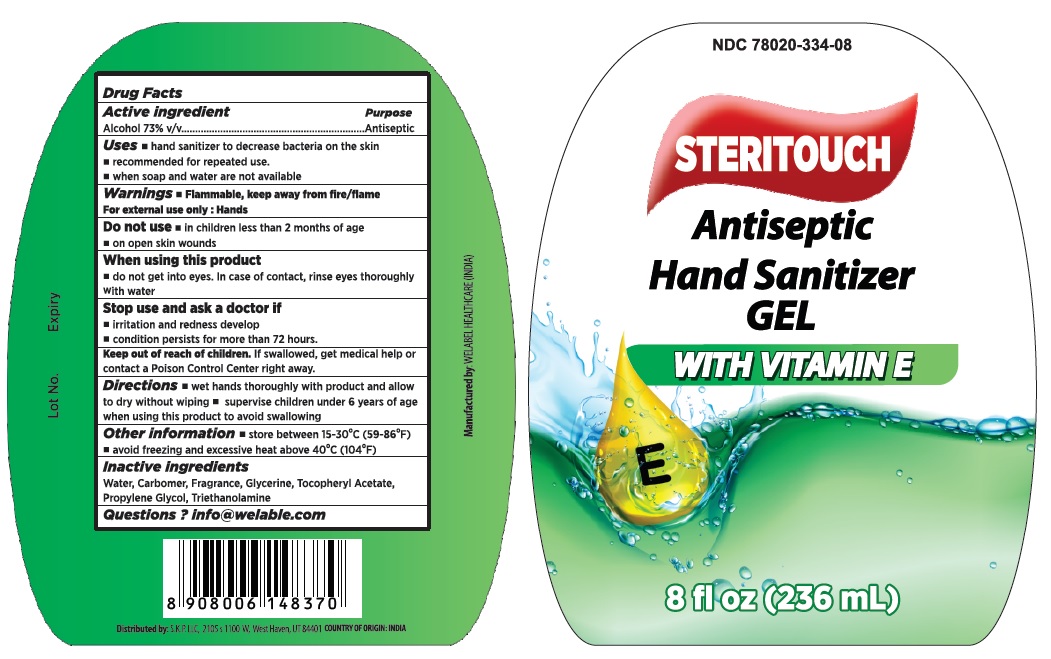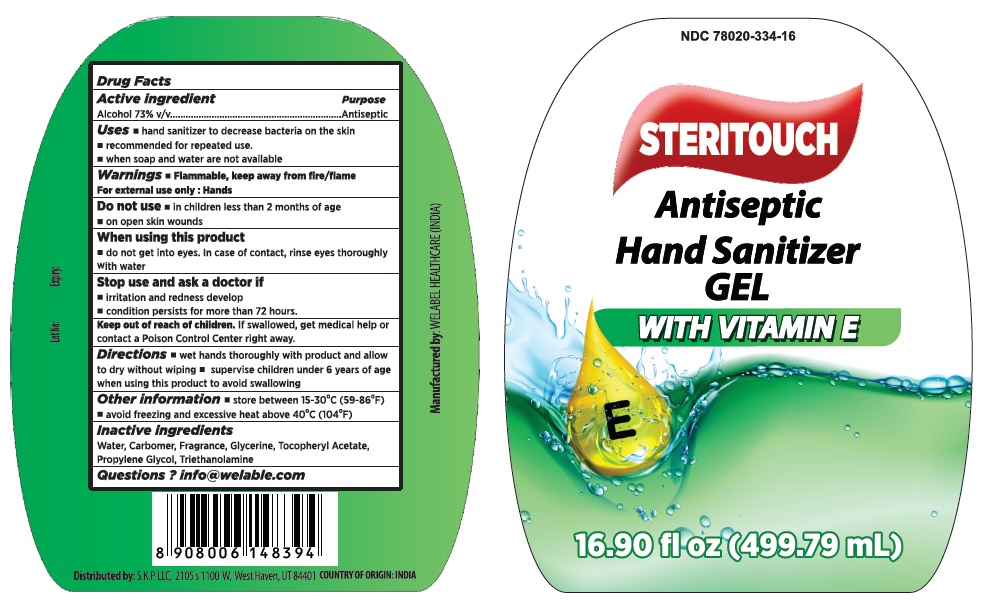 DRUG LABEL: STERITOUCH Antiseptic Hand Sanitizer WITH VITAMIN E
NDC: 78020-334 | Form: GEL
Manufacturer: WELABLE HEALTHCARE
Category: otc | Type: HUMAN OTC DRUG LABEL
Date: 20201105

ACTIVE INGREDIENTS: ALCOHOL 73 mL/100 mL
INACTIVE INGREDIENTS: WATER; CARBOMER HOMOPOLYMER, UNSPECIFIED TYPE; GLYCERIN; .ALPHA.-TOCOPHEROL ACETATE; PROPYLENE GLYCOL; TROLAMINE

STERITOUCH Antiseptic Hand Sanitizer GEL

Active ingredient

Alcohol 73% v/v

Purpose

Antiseptic

Uses

• hand sanitizer to decrease bacteria on the skin

• recommended for repeated use

• when soap and water are not available

Warnings

Flammable, keep away from fire/flame

For external use only

Do not use

• in children less than 2 months of age

• on open skin wounds

When using this product

• do not get into eyes. In case of contact, rinse eyes thoroughly with water

Stop use and ask a doctor if

• irritation and redness develop

• condition persists for more than 72 hours

Keep out of reach of children. If swallowed, get medical help or contact a Poison Control Center right away.

Directions

• wet hands thoroughly with product and allow to dry without wiping

• supervise children under 6 years of age when using this product to avoid swallowing

Other information

• store between 15-30°C (59-86°F)

• avoid freezing and excessive heat above 40°C (104°F)

Inactive ingredients

Water, Carbomer, Fragrance, Glycerine, Tocopheryl Acetate, Propylene Glycol, Triethanolamine

Questions? +1-801-392-0937

You may also report serious side effects to this phone number.

Mon-Fri 9:00 AM - 5:00 PM

Distributed by: S.K.P. LLC, 2105 s 1100 W, West Haven, UT 84401

COUNTRY OF ORIGIN: INDIA

Manufactured by: WELABLE HEALTHCARE(INDIA)

E-Mail: info@welable.com